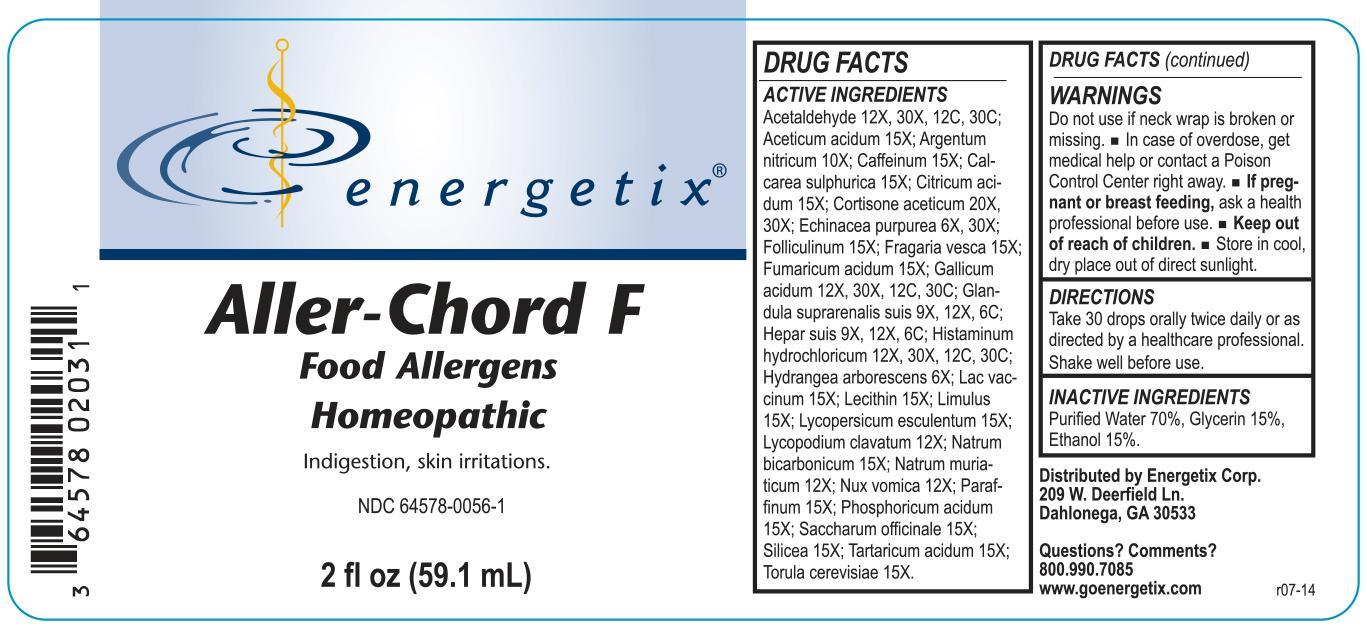 DRUG LABEL: Aller-Chord Food
NDC: 64578-0056 | Form: LIQUID
Manufacturer: Energetix Corp
Category: homeopathic | Type: HUMAN OTC DRUG LABEL
Date: 20140402

ACTIVE INGREDIENTS: ACETALDEHYDE 12 [hp_X]/59.1 mL; SUS SCROFA ADRENAL GLAND 9 [hp_X]/59.1 mL; SILVER NITRATE 10 [hp_X]/59.1 mL; CORTISONE ACETATE 20 [hp_X]/59.1 mL; GALLIC ACID MONOHYDRATE 12 [hp_X]/59.1 mL; HISTAMINE DIHYDROCHLORIDE 12 [hp_X]/59.1 mL; ECHINACEA PURPUREA 6 [hp_X]/59.1 mL; HYDRANGEA ARBORESCENS ROOT 6 [hp_X]/59.1 mL; PORK LIVER 9 [hp_X]/59.1 mL; LYCOPODIUM CLAVATUM SPORE 12 [hp_X]/59.1 mL; STRYCHNOS NUX-VOMICA SEED 12 [hp_X]/59.1 mL; ACETIC ACID 15 [hp_X]/59.1 mL; CAFFEINE 15 [hp_X]/59.1 mL; CALCIUM SULFATE ANHYDROUS 15 [hp_X]/59.1 mL; ANHYDROUS CITRIC ACID 15 [hp_X]/59.1 mL; FUMARIC ACID 15 [hp_X]/59.1 mL; COW MILK 15 [hp_X]/59.1 mL; EGG PHOSPHOLIPIDS 15 [hp_X]/59.1 mL; SODIUM BICARBONATE 15 [hp_X]/59.1 mL; SUCROSE 15 [hp_X]/59.1 mL; TARTARIC ACID 15 [hp_X]/59.1 mL; SACCHAROMYCES CEREVISIAE 15 [hp_X]/59.1 mL; SODIUM CHLORIDE 12 [hp_X]/59.1 mL; PARAFFIN 15 [hp_X]/59.1 mL; ESTRONE 15 [hp_X]/59.1 mL; PHOSPHORIC ACID 15 [hp_X]/59.1 mL; ALPINE STRAWBERRY 15 [hp_X]/59.1 mL; LIMULUS POLYPHEMUS 15 [hp_X]/59.1 mL; SOLANUM LYCOPERSICUM 15 [hp_X]/59.1 mL; SILICON DIOXIDE 15 [hp_X]/59.1 mL
INACTIVE INGREDIENTS: ALCOHOL 41.36 mL/59.1 mL; GLYCERIN 8.86 mL/59.1 mL; WATER 8.86 mL/59.1 mL

Aller-Chord F

ACTIVE INGREDIENT

Acetaldehyde 12X, 30X, 12C, 30C; Aceticum acidum 15X; Argentum nitricum 10X; Caffeinum 15X; Calcarea sulphurica 15X; Citricum acidum 15X; Cortisone aceticum 20X, 30X; Echinacea purpurea 6X, 30X; Folliculinum 15X; Fragaria vesca 15X; Fumaricum acidum 15X; Gallicum acidum 12X, 30X, 12C, 30C; Glandula suprarenalis suis 9X, 12X, 6C; Hepar suis 9X, 12X, 6C; Histaminum hydrochloricum 12X, 30X, 12C, 30C; Hydrangea arborescens 6X; Lac vaccinum 15X; Lecithin 15X; Limulus 15X; Lycopersicum esculentum 15X; Lycopodium clavatum 12X; Natrum bicarbonicum 15X; Natrum muriaticum 12X; Nux vomica 12X; Paraffinum 15X; Phosphoricum acidum 15X; Saccharum officinale 15X; Silicea 15X; Tartaricum acidum 15X; Torula cerevisiae 15X

Do not use if neck wrap is broken or missing.

OVERDOSAGE

In case of overdose, get medical help or contact a Poison Control Center right away.

PREGNANCY OR BREAST FEEDING

If pregnant or breast feeding, ask a health professional before use.

Keep out of reach of children.

STORAGE AND HANDLING

Store in cool, dry place out of direct sunlight.

Questions? Comments?

800.990.7085 www.goenergetix.com

PURPOSE

Indigestion, skin irritations.

INACTIVE INGREDIENT

Purified Water 70%, Glycerin 15%, Ethanol 15%.

DOSAGE AND ADMINISTRATION

Take 30 drops orally twice daily or as directed by a healthcare professional. Shake well before use.

INDICATIONS AND USAGE

Indigestion, skin irritations.